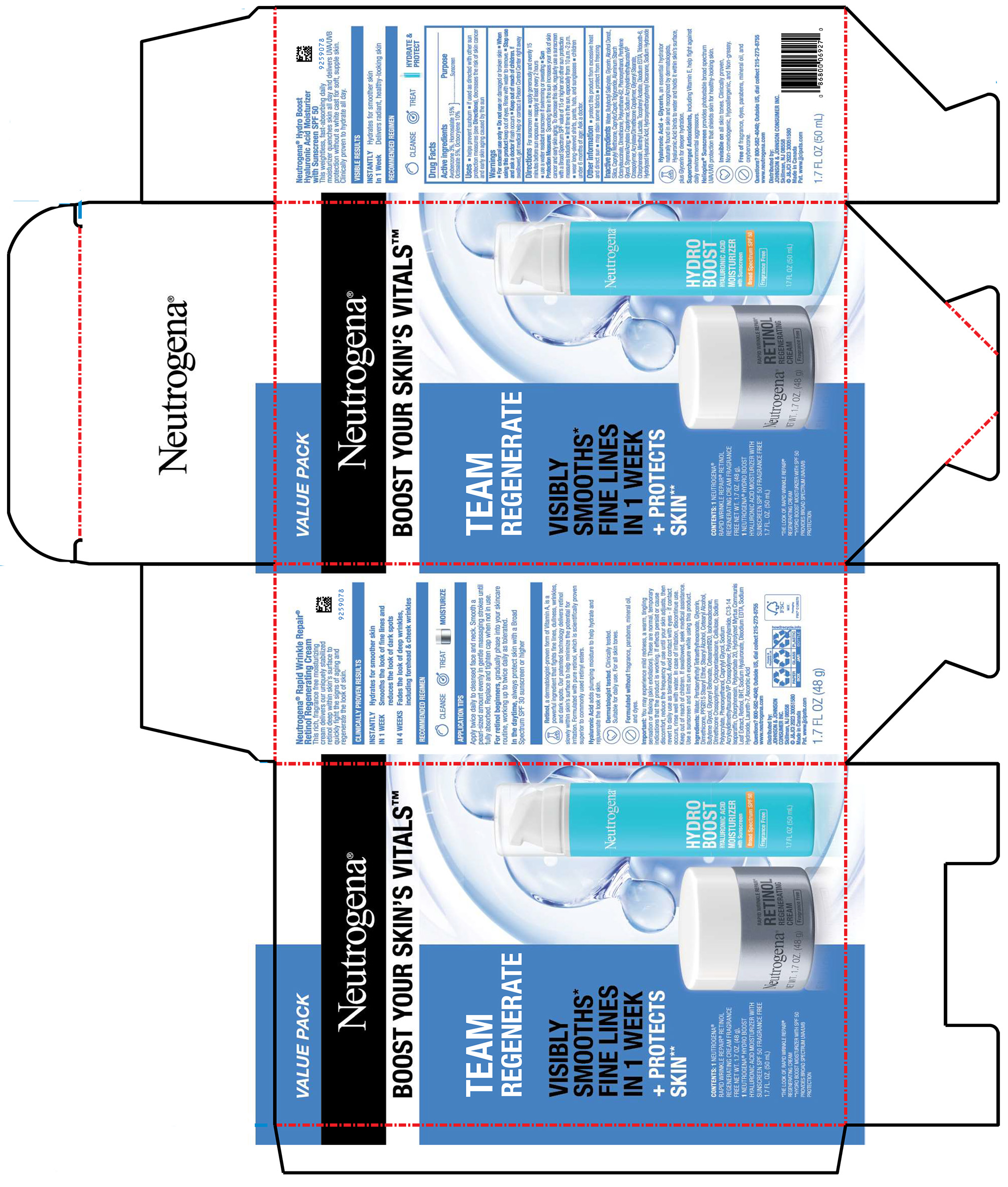 DRUG LABEL: Neutrogena Boost Your Skins Vitals Team Regenerate
NDC: 69968-0845 | Form: KIT | Route: TOPICAL
Manufacturer: Kenvue Brands LLC
Category: otc | Type: HUMAN OTC DRUG LABEL
Date: 20251106

ACTIVE INGREDIENTS: OCTOCRYLENE 100 mg/1 mL; AVOBENZONE 30 mg/1 mL; HOMOSALATE 150 mg/1 mL; OCTISALATE 50 mg/1 mL
INACTIVE INGREDIENTS: HYALURONIC ACID; SILICON DIOXIDE; CAPRYLYL TRISILOXANE; 1-(4-HYDROXY-3-METHOXYPHENYL)-DECAN-3-ONE; SODIUM HYDROXIDE; MEDIUM-CHAIN TRIGLYCERIDES; ALUMINUM STARCH OCTENYLSUCCINATE; DIMETHICONE; PENTYLENE GLYCOL; GLYCERIN; CHLORPHENESIN; MENTHYL LACTATE, (-)-; WATER; BUTYLOCTYL SALICYLATE; ALCOHOL; POLYURETHANE-62; PHENOXYETHANOL; BUTYL METHACRYLATE/METHYL METHACRYLATE/METHACRYLIC ACID/STYRENE CROSSPOLYMER; GLYCERYL MONOSTEARATE; ALPHA-TOCOPHEROL ACETATE; EDETATE DISODIUM ANHYDROUS; TRIDECETH-6

Neutrogena Boost Your Skins Vitals Team Regenerate

Neutrogena Hydro Boost Hyaluronic Acid Moisturizer with Sunscreen Broad Spectrum SPF 50

Drug Facts

Active ingredients

Avobenzone 3%

Homosalate 15%

Octisalate 5%

Octocrylene 10%

Purpose

Sunscreen

Uses

- helps prevent sunburn
- if used as directed with other sun protection measures (see Directions), decreases the risk of skin cancer and early skin aging caused by the sun

Warnings

For external use only

Do not use on damaged or broken skin

When using this product keep out of eyes. Rinse with water to remove.

Stop use and ask a doctor if rash occurs

Keep out of reach of children. If swallowed, get medical help or contact a Poison Control Center right away

Directions

For sunscreen use:

- apply generously and evenly 15 minutes before sun exposure
- reapply at least every 2 hours
- use a water resistant sunscreen if swimming or sweating
- Sun Protection Measures: Spending time in the sun increases your risk of skin cancer and early skin aging. To decrease this risk, regularly use a sunscreen with a Broad Spectrum SPF value of 15 or higher and other sun protection measures including:
  - limit time in the sun, especially from 10 a.m.-2 p.m.
  - wear long-sleeved shirts, pants, hats, and sunglasses
- children under 6 months of age: Ask a doctor.

Other information

- protect this product from excessive heat and direct sun
- may stain some fabrics
- protect from freezing

Inactive ingredients

Water, Butyloctyl Salicylate, Glycerin, Alcohol Denat., Silica, Caprylyl Methicone, Caprylic/Capric Triglyceride, Aluminum Starch Octenylsuccinate, Dimethicone, Polyurethane-62, Phenoxyethanol, Pentylene Glycol, Styrene/Acrylates Copolymer, Sodium Acryloyldimethyltaurate/VP Crosspolymer, Acrylates/Dimethicone Copolymer, Glyceryl Stearate, Chlorphenesin, Menthyl Lactate, Tocopheryl Acetate, Disodium EDTA, Trideceth-6, Hydrolyzed Hyaluronic Acid, Hydroxymethoxyphenyl Decanone, Sodium Hydroxide

Questions?

Call toll-free 800-582-4048 or 215-273-8755 (collect) or visit www.neutrogena.com

Distributed by:
JOHNSON & JOHNSON CONSUMER INC.
Skillman, NJ 08558

PRINCIPAL DISPLAY PANEL - Kit Package

VALUE PACK

Neutrogena®

BOOST YOUR SKIN’S VITALS™

TEAM

REGENERATE

VISIBLY

SMOOTHS*

FINE LINES

IN 1 WEEK

+ PROTECTS

SKIN**

CONTENTS: 1 NEUTROGENA®

RAPID WRINKLE REPAIR® RETINOL

REGENERATING CREAM FRAGRANCE

FREE NET WT. 1.7 OZ. (48 g),

1 NEUTROGENA® HYDRO BOOST

HYALURONIC ACID MOISTURIZER WITH

SUNSCREEN SPF 50 FRAGRANCE FREE

1.7 FL. OZ. (50 mL)

*THE LOOK OF RAPID WRINKLE REPAIR®

REGENERATING CREAM

**HYDRO BOOST MOISTURIZER WITH SPF 50

PROVIDES BROAD SPECTRUM UVA/UVB

PROTECTION